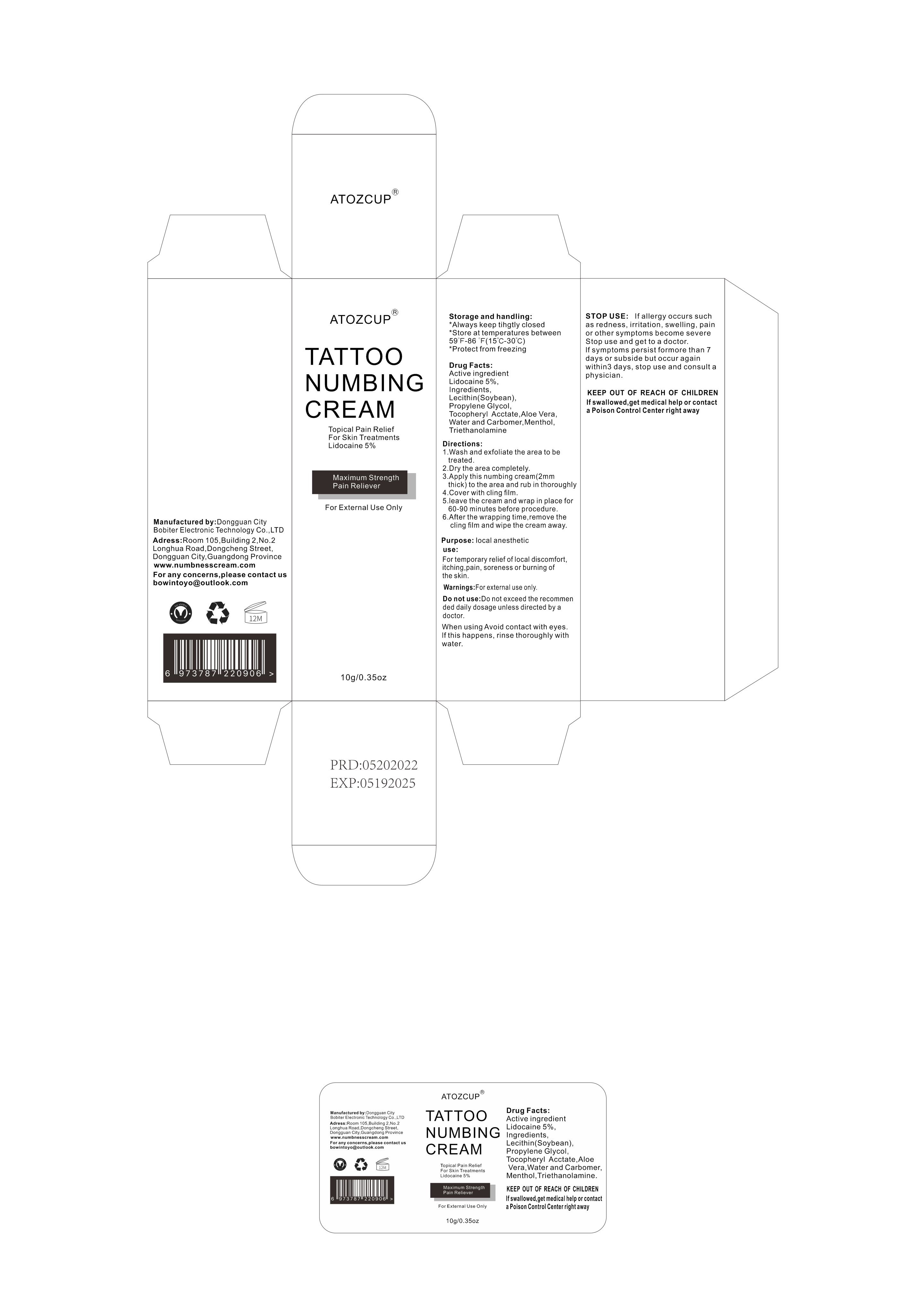 DRUG LABEL: ATOZCUP TATTOO NUMBING
NDC: 83706-001 | Form: CREAM
Manufacturer: Dongguan City Bobiter Electronic Technology Co., Ltd
Category: otc | Type: HUMAN OTC DRUG LABEL
Date: 20231220

ACTIVE INGREDIENTS: LIDOCAINE 5 g/100 g
INACTIVE INGREDIENTS: PROPYLENE GLYCOL; CARBOMER HOMOPOLYMER TYPE B (ALLYL SUCROSE CROSSLINKED); ALOE VERA LEAF; WATER; LECITHIN, SOYBEAN; .ALPHA.-TOCOPHEROL ACETATE; MENTHOL, UNSPECIFIED FORM; TROLAMINE

Active Ingredient(s)

Lidocaine 5%

Purpose

local anesthetic

Use

For temporary relief of local discomfort, itching, pain,soreness or burning of the skin

Warnings

For external use only.

Do not use

Do not exceed the recommended daily dosage unless directed by a doctor.

WHEN USING

When using Avoid contact with eyes. If this happens, rinse thoroughly with water.

STOP USE

lf allergy occurs such as redness,irritation,swelling,pain or other symptoms become severe Stop use and get to a doctor.If symptoms persist for more than 7days or subside but occur again within3 days,stop use and consult aphysician.

Keep out of reach of children.

Directions

1.Wash and exfoliate the area to be treated.
2.Dry the area completely.

3.Apply this numbing cream(2mm thick) to the area and rub in thoroughly

4.Cover with cling film.

5.leave the cream and wrap in place for 60-90 minutes before procedure.

6.After the wrapping time,remove thecling film and wipe the cream away

Storage and handling

*Always keep tihgtly closed

*Store at temperatures between 59°F-86°F(15°C-30°C)

*Protectfrom freezing

Inactive ingredients

Lecithin(Soybean)，Propylene Glycol，Tocopheryl Acctate,Aloe Vera，Water，Carbomer,Menthol，Triethanolamine